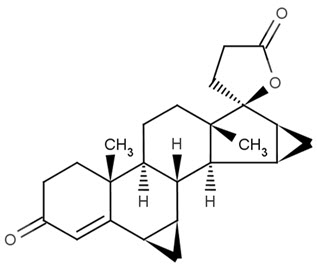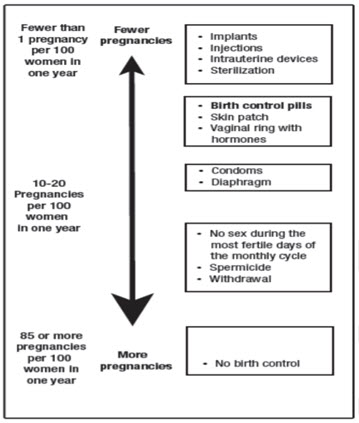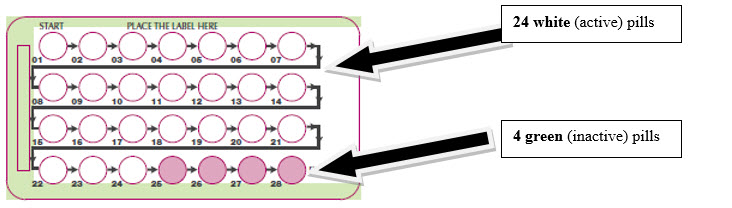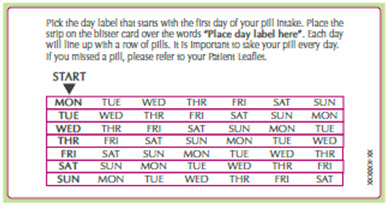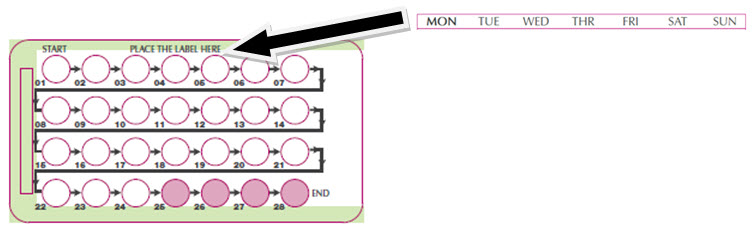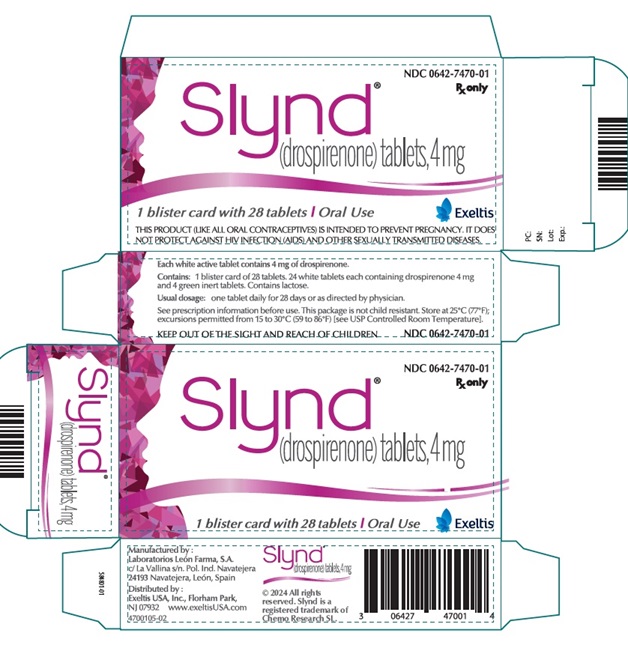 DRUG LABEL: SLYND
NDC: 0642-7470 | Form: KIT | Route: ORAL
Manufacturer: Exeltis USA, Inc.
Category: prescription | Type: HUMAN PRESCRIPTION DRUG LABEL
Date: 20250701

ACTIVE INGREDIENTS: DROSPIRENONE 4 mg/1 1
INACTIVE INGREDIENTS: TALC; MAGNESIUM STEARATE; POLYETHYLENE GLYCOL 3350; POLYVINYL ALCOHOL, UNSPECIFIED; TITANIUM DIOXIDE; MICROCRYSTALLINE CELLULOSE; SILICON DIOXIDE; ANHYDROUS LACTOSE; STARCH, CORN; MAGNESIUM STEARATE; TITANIUM DIOXIDE; SILICON DIOXIDE; ANHYDROUS LACTOSE; POVIDONE K30; HYPROMELLOSE 2910 (15 MPA.S); TRIACETIN; FERRIC OXIDE YELLOW; POLYSORBATE 80; FD&C BLUE NO. 2 ALUMINUM LAKE

HIGHLIGHTS OF PRESCRIBING INFORMATION

These highlights do not include all the information needed to use SLYND safely and effectively. See full prescribing information for SLYND.
SLYND® (drospirenone) tablets, for oral use
Initial U.S. Approval: 2001

1 INDICATIONS AND USAGE

SLYND is a progestin indicated for use by females of reproductive potential to prevent pregnancy. (1)

2 DOSAGE AND ADMINISTRATION

Take one tablet taken daily for 28 days; one white active tablet daily during the first 24 days and one green inactive tablet daily during the 4 following days. (2)

3 DOSAGE FORMS AND STRENGTHS

SLYND consists of 24 white tablets each containing 4 mg of drospirenone and 4 green inert tablets. (3)

4 CONTRAINDICATIONS

- Renal impairment (4)
- Adrenal insufficiency (4)
- Presence or history of progestin sensitive cancers (4)
- Liver tumors, benign or malignant, or hepatic impairment (4)
- Undiagnosed abnormal uterine bleeding (4)

5 WARNINGS AND PRECAUTIONS

- Hyperkalemia: Check serum potassium levels during the first treatment cycle in females receiving daily, long-term treatment for chronic conditions of diseases with medications that may increase serum potassium concentrations. (5.1)
- Thromboembolic disorders: Discontinue SLYND if a thromboembolic event occurs. (5.2)
- Bone loss: It is unknown if SLYND may cause a clinically relevant loss of bone mineral density. (5.3)
- Liver Disease: Discontinue use if jaundice or acute or chronic disturbances of liver function develop. (5.5)
- Ectopic pregnancy: Be alert to the possibility of ectopic pregnancy in females who become pregnant or complain of lower abdominal pain while on SLYND. (5.6)
- Risk of Hyperglycemia in Patients with Diabetes: Patients with diabetes may be at greater risk of hyperglycemia and may require additional medication adjustments or monitoring. (5.7)
- Bleeding Irregularities and Amenorrhea: May cause irregular bleeding or amenorrhea. Evaluate for other causes, such as pregnancy, if irregular bleeding or amenorrhea persists. (5.8)

6 ADVERSE REACTIONS

Most common adverse reactions (>1%) are: acne, metrorrhagia, headache, breast pain, weight increased, dysmenorrhea, nausea, vaginal hemorrhage, libido decreased, breast tenderness, menstruation irregular (6)

To report SUSPECTED ADVERSE REACTIONS, contact Exeltis USA, Inc. at 1-877-324-9349 or FDA at 1-800-FDA-1088 or www.fda.gov/medwatch.

7 DRUG INTERACTIONS

Drugs or herbal products that induce certain enzymes (for example, CYP3A4) may decrease the effectiveness of SLYND or increase breakthrough bleeding. Counsel patients to use a back-up or alternative method of contraception when enzyme inducers are used with SLYND. (7.1)

8 USE IN SPECIFIC POPULATIONS

- Pregnancy: Discontinue SLYND if pregnancy occurs (8.1)

FULL PRESCRIBING INFORMATION

1 INDICATIONS AND USAGE

SLYND is a progestin indicated for use by females of reproductive potential to prevent pregnancy.

2 DOSAGE AND ADMINISTRATION

2.1 How to Use SLYND

SLYND is dispensed in a blister card. SLYND should be started using a Day 1 start.

Table 1 Instructions for Starting or Switching SLYND
Starting SLYND in females with no current use of hormonal contraception (Day 1 Start) Important: Consider the possibility of ovulation and conception prior to initiation of this product. Tablet Color: • SLYND active tablets are white (Day 1 to Day 24). • SLYND inert tablets are green (Day 25 to Day 28). | Day 1 Start: • Take first white active tablet on the first day of menses. • Take subsequent white active tablets once daily at the same time each day for a total of 24 days. • Take one green inert tablet daily for 4 days and at the same time of day that active tablets were taken. • Begin each subsequent pack on the same day of the week as the first cycle pack (i.e., on the day after taking the last inactive tablet).
Switching from another contraceptive method to SLYND | Start SLYND:
- A Combined Oral Contraceptive (COC) | - On the day when the new pack of the previous COC would have started.
- Transdermal Patch | - On the day when next application would have been scheduled.
- Vaginal ring | - On the day when next insertion would have been scheduled.
- Injection | - On the day when next injection would have been scheduled.
- Intrauterine contraceptive | - On the day of removal
- Implant | - On the day of removal
Refer to the Patient Information and Instructions for Use for additional instructions for counseling patient concerning proper use

2.2 How to Take SLYND

SLYND (white active and green inert tablets) is swallowed whole once a day. Take one tablet daily for 28 consecutive days; one white active tablet daily during the first 24 days and one green inert tablet daily during the 4 following days. Tablets must be taken every day at about the same time of the day so that the interval between two tablets is always 24 hours.

2.3 Missed Doses

Table 2 Instructions for Missed SLYND
- If one white active tablet is missed | Take the missed tablet as soon as possible. Continue taking one tablet a day until the pack is finished.
- If two or more white active tablets are missed | Take the last missed tablet as soon as possible. Continue one tablet a day until the pack is finished (one or more missed tablet(s) will remain in the blister pack). Additional non-hormonal contraception (such as condoms or spermicide) should be used as back-up if the patient has sex within 7 days after missing tablets.
- If one or more green inert tablets are missed | Skip the missed pill days and continue taking one tablet a day until the pack is finished.

2.4 Advice in Case of Gastrointestinal Disturbances

If vomiting or diarrhea occurs within 3-4 hours after tablet taking, the new tablet (scheduled for the next day) should be taken as soon as possible. The new tablet should be taken within 12 hours of the usual time of tablet-taking if possible. If more than two tablets are missed, the advice concerning missed tablets, including using backup non-hormonal contraception, given above is applicable.

3 DOSAGE FORMS AND STRENGTHS

SLYND is supplied in blister cards, each containing 24 round, film-coated, unscored, white tablets and 4 round, film-coated, unscored green tablets.

- Each white tablet contains 4 mg of drospirenone. White tablets are debossed with an "E" on one side and a "D" on the other side
- Each green tablet is inert and does not contain drospirenone. Green tablets are debossed with an "E" on one side and a "4" on the other side.

4 CONTRAINDICATIONS

SLYND is contraindicated in females with the following conditions:

- Renal impairment [see Warnings and Precautions (5.1) and Use in Specific Populations (8.7)]
- Adrenal insufficiency [see Warnings and Precautions (5.1)]
- Presence or history of cervical cancer or progestin sensitive cancers [see Warnings and Precautions (5.4)]
- Liver tumors, benign or malignant, or hepatic impairment [see Warnings and Precautions (5.5) and Use in Specific Populations (8.6)]
- Undiagnosed abnormal uterine bleeding [see Warnings and Precautions (5.8)]

5 WARNINGS AND PRECAUTIONS

5.1 Hyperkalemia

SLYND contains drospirenone, a progestin, which has anti-mineralocorticoid activity, including the potential for hyperkalemia in high-risk females, comparable to a 25 mg dose of spironolactone. SLYND is contraindicated in females with conditions that predispose to hyperkalemia (e.g. renal impairment, hepatic impairment, and adrenal insufficiency). Females receiving daily, long-term treatment for chronic conditions or diseases with medications that may increase serum potassium concentration should have their serum potassium concentration checked prior to starting treatment and during the first treatment cycle. Consider monitoring serum potassium concentration in females at increased risk for hyperkalemia i.e., those females who take a strong CYP3A4 inhibitor long-term and concomitantly with SLYND. Strong CYP3A4 inhibitors include azole antifungals (e.g. ketoconazole, itraconazole, voriconazole), HIV/HCV protease inhibitors (e.g., indinavir, boceprevir), and clarithromycin [see Drug Interactions (7)] . Monitor females taking SLYND who later develop medical conditions and/or begin medication that put them at an increased risk for hyperkalemia.

Most females with hyperkalemia in the clinical development studies of SLYND had mild potassium elevations and/or isolated increases that returned to normal while still on study medication. No concurrent adverse reactions were attributed to hyperkalemia. In the pivotal trial, two females (0.2%) with persistent potassium elevations discontinued SLYND.

5.2 Thromboembolic Disorders

Epidemiological studies have not indicated an association between progestin-only preparations and an increased risk of myocardial infarction, cerebral thromboembolism, or venous thromboembolism.

Combined oral contraceptives containing drospirenone and ethinyl estradiol may be associated with a higher risk of venous thromboembolism (VTE) than those containing some other progestins in combination with ethinyl estradiol. It is unknown whether the risk of VTE is increased with drospirenone alone; however, if there is a risk, it is expected to be lower than that of drospirenone in combination with ethinyl estradiol.

When prescribing SLYND, consider the increased risk of thromboembolism inherent in the postpartum period and in females with a history of thromboembolism.

Discontinue SLYND if arterial or venous thromboembolic events occur. Consider discontinuing SLYND, if feasible, in case of prolonged immobilization due to surgery or illness.

5.3 Bone Loss

Treatment with SLYND leads to decreased estradiol serum levels. It is unknown if this may cause a clinically relevant loss of bone mineral density.

5.4 Cervical Cancer

Some studies suggest that use of combination hormonal contraceptives containing progestin and estradiol has been associated with an increase in the risk of cervical cancer or intraepithelial neoplasia. However, there continues to be controversy about the extent to which such findings may be due to differences in sexual behavior and other factors.

5.5 Liver Disease

Discontinue SLYND if jaundice or acute or chronic disturbances of liver function develop. Do not resume use until markers of liver function return to normal and SLYND causation has been excluded.

SLYND is contraindicated in females with liver tumors, benign or malignant, or hepatic impairment [see Use in Specific Populations (8.6)].

5.6 Ectopic Pregnancy

Be alert to the possibility of ectopic pregnancy in females who become pregnant or complain of lower abdominal pain while on SLYND.

5.7 Risk of Hyperglycemia in Patients with Diabetes

Some patients receiving progestins, including SLYND, may exhibit a decrease in insulin sensitivity. Therefore, patients with diabetes may be at greater risk of hyperglycemia and may require additional medication adjustments or monitoring.

5.8 Bleeding Irregularities and Amenorrhea

Females using SLYND may experience unscheduled (breakthrough or intracyclic) bleeding and spotting, especially during the first three months of use. Bleeding irregularities may resolve over time or by changing to a different contraceptive product. If bleeding persists or occurs after previously regular cycles, evaluate for causes such as pregnancy or malignancy.

Based on subject diaries from four clinical trials of SLYND, 64.4% of females experienced unscheduled bleeding at Cycle 1. This percentage decreased to 40.3% by Cycle 13.

A total of 91 out of 2593 subjects (3.5%) discontinued SLYND due to menstrual bleeding disorders including metrorrhagia, menstrual irregular, vaginal hemorrhage, menorrhagia, uterine hemorrhage, and amenorrhea.

If scheduled bleeding does not occur, consider the possibility of pregnancy. If the patient has not adhered to the prescribed dosing schedule (missed one or two active tablets or started taking them on a day later than she should have, consider the possibility of pregnancy at the time of the first missed period and perform appropriate diagnostic measures. If the patient has adhered to the prescribed dosing schedule and misses two consecutive periods, rule out pregnancy.

5.9 Depression

Carefully observe females for a history of depression and discontinue SLYND if depression recurs to a serious degree. Data on the association of progestin-only contraceptive products with onset of depression and exacerbation of depression are limited.

6 ADVERSE REACTIONS

The following clinically significant adverse reactions are described elsewhere in other sections of the labeling:

- Hyperkalemia [see Warnings and Precautions (5.1)]
- Bleeding Irregularities and Amenorrhea [see Warnings and Precautions (5.8)]

Because clinical trials are conducted under widely varying conditions, adverse reaction rates observed in the clinical trials of a drug cannot be directly compared to rates in the clinical trials of another drug and may not reflect the rates observed in practice.

The data described below reflect the exposure of SLYND in females of reproductive potential desiring to prevent pregnancy based on four clinical studies including Study CF111/303 [see Clinical Studies (14)]. The mean time of SLYND exposure ranged from 197 to 328 days. The demographic profile for the pooled study data was: mean age 28 years; mean BMI 25 kg/m^2; racial distribution was 83% White; 14% Black; 1% Asian and 2% Other.

Table 3 Adverse Reactions Occurring in ≥ 1% of Females Receiving SLYND in Four Pooled Studies
Adverse Reaction | Total N = 2598 n (%)
Any adverse reaction | 627 (24.1)
Acne | 98 (3.8)
Metrorrhagia | 72 (2.8)
Headache | 71 (2.7)
Breast pain | 57 (2.2)
Weight increased | 50 (1.9)
Dysmenorrhea | 49 (1.9)
Nausea | 47 (1.8)
Vaginal hemorrhage | 45 (1.7)
Libido decreased | 33 (1.3)
Breast tenderness | 31 (1.2)
Menstruation irregular | 30 (1.2)

7 DRUG INTERACTIONS

Consult the labeling of all concurrently-used drugs to obtain further information about interactions with hormonal contraceptives or the potential for enzyme alterations.

7.1 Effects of other Drugs on Hormonal Contraceptives

Substances decreasing the systemic concentrations of hormonal contraceptives (HCs) and potentially diminishing the efficacy of HCs:

Drugs or herbal products that induce certain enzymes, including cytochrome P450 3A4 (CYP3A4), may decrease the systemic concentrations of HCs and potentially diminish the effectiveness of HCs or increase breakthrough bleeding.

Some drugs or herbal products that may decrease the effectiveness of HCs include efavirenz, phenytoin, barbiturates, carbamazepine, bosentan, felbamate, griseofulvin, oxcarbazepine, rifampicin, rifabutin, rufinamide, aprepitant, and products containing St. John's wort.

Interactions between HCs and other drugs may lead to breakthrough bleeding and/or contraceptive failure. Counsel females to use an alternative non-hormonal method of contraception or a back-up method when enzyme inducers are used with HCs, and to continue back-up non-hormonal contraception for 28 days after discontinuing the enzyme inducer to ensure contraceptive reliability.

Substances increasing the systemic concentrations of hormonal contraceptives (HCs):

In a clinical drug-drug interaction study conducted in premenopausal females, once daily co-administration of drospirenone (DRSP) 3 mg/ethinyl estradiol (EE) 0.02 mg containing tablets with strong CYP3A4 inhibitor, ketoconazole 200 mg twice daily for 10 days, resulted in a moderate increase of DRSP systemic exposure.

7.2 Influence of SLYND on other Medicinal Products

Based on in vitro studies and in vivo interaction studies in female volunteers using omeprazole, simvastatin and midazolam as marker substrate, an interaction of drospirenone with the metabolism of other active substances is unlikely.

Potential to increase serum potassium concentration:

There is a potential for an increase in serum potassium concentration in females taking SLYND with other drugs that may increase serum potassium concentration (for example, ACE inhibitors, angiotensin-II receptor antagonists, potassium-sparing diuretics, potassium supplementation, heparin, aldosterone antagonists, and NSAIDS [see Warnings and Precautions (5.1)].

8 USE IN SPECIFIC POPULATIONS

8.1 Pregnancy

Risk Summary

Based on epidemiologic studies and meta-analyses, there is little or no increased risk of birth defects in the children of females who inadvertently use oral progestins during early pregnancy (See Data).

Discontinue SLYND if pregnancy occurs, because there is no reason to use hormonal contraceptives during pregnancy

In the U.S. general population, the estimated background risk of major birth defects and miscarriage in clinically recognized pregnancies is 2 to 4 percent and 15 to 20 percent, respectively.

Data

Human Data

Epidemiologic studies and meta-analyses have not found an increased risk of genital or nongenital birth defects (including cardiac anomalies and limb-reduction defects) following maternal use of oral progestins before conception or during early pregnancy.

8.2 Lactation

Risk Summary

Negligible amounts of drospirenone are excreted in the breast milk (see Data) . Thus, at therapeutic doses of SLYND, no effects on breastfed newborns/infants are anticipated. In general, no adverse effects have been found on milk production or on the health, growth, or development of the infant with use of progestin-only pills (POPs).

Human Data

After daily administration of 4 mg SLYND tablets, the average DRSP concentration in breast milk over a 24-hour period is 5.6 ng/mL. Based on this concentration, the estimated average infant daily dosages for an exclusively breastfed infant is 840 ng/kg/day (relative infant dose is 1.5%).

8.4 Pediatric Use

Safety and efficacy of SLYND have been established in females of reproductive age. Safety and efficacy are expected to be the same for postpubertal adolescents under the age of 16 and users 16 years and older.

Study CF111/304 evaluated the bleeding associated with SLYND in females ≥12 years of age. Bleeding data were generally consistent with those from Study CF111/303 in adult females [see Clinical Studies (14)] .

Use of this product before menarche is not indicated.

8.5 Geriatric Use

SLYND has not been studied in postmenopausal females and is not indicated in this population.

8.6 Hepatic Impairment

SLYND is contraindicated in females with hepatic impairment [see Contraindications (4), Warnings and Precautions (5.5)]. The mean exposure to drospirenone in females with moderate liver impairment is approximately three times higher than the exposure in females with normal liver function. SLYND has not been studied in females with severe hepatic impairment [see Clinical Pharmacology (12.3)] .

8.7 Renal Impairment

SLYND is contraindicated in females with renal impairment [see Contraindications (4), Warnings and Precautions (5.1)].

In subjects with creatinine clearance (CLcr) of 50–79 mL/min, serum DRSP levels were comparable to those in a control group with CLcr ≥ 80 mL/min. In subjects with CLcr of 30–49 mL/min, serum DRSP concentrations were on average 37% higher than those in the control group. In addition, there is a potential to develop hyperkalemia in subjects with renal impairment whose serum potassium is in the upper reference range, and who are concomitantly using potassium sparing drugs [see Drug Interactions (7.2) and Clinical Pharmacology (12.3)].

10 OVERDOSAGE

There have been no reports of serious deleterious effects from overdosage of SLYND. Symptoms that may occur include nausea, vomiting, and vaginal bleeding. There are no antidotes and treatment should be to provide symptomatic support.

Drospirenone is a spironolactone analogue which has anti-mineralocorticoid properties. Therefore, serum potassium and sodium, and evidence of metabolic acidosis, should be monitored in cases of overdose.

11 DESCRIPTION

SLYND (drospirenone) is for use as an oral contraceptive. It is supplied as clear to a slightly opaque PVC-PVDC/Aluminum blister cards, each holding of 24 white tablets each containing 4 mg of drospirenone, a synthetic progestational compound and 4 green inert tablets.

Drospirenone is chemically described as (6R,7R,8R,9S,10R,13S,14S,15S,16S,17S)-1,3',4',6,6a,7,8,9,10,11, 12,13,14,15,15a,16-hexadecahydro10,13-dimethylspiro-[17H-dicyclopropa- [6,7:15,16]cyclopenta[a]phenanthrene-17,2'(5H)-furan]-3,5'(2H)-dione). It has a molecular weight of 366.5, a molecular formula of C24H30O3, and the structural formula below:

Drospirenone is a white to almost white or slightly yellow crystalline powder. It is a progestin and neutral molecule with slight solubility in water

The active tablet is a 5 mm, round, unscored, film-coated, white tablet that contains 4mg of drospirenone as the active ingredient, and microcrystalline cellulose NF, anhydrous lactose NF, colloidal silicon dioxide NF, magnesium stearate NF, polyvinyl alcohol partially hydrolyzed NF, talc NF, titanium dioxide NF, and polyethylene glycol NF as the inactive ingredients. Each tablet is debossed with the letter "E" on one side and the letter "D" on the other side.

The inert tablet is a 5 mm, round, unscored, film-coated, green tablet that does not contain drospirenone. Each inert green tablet contains the following inactive ingredients: lactose monohydrate NF, corn starch NF, povidone 30000 NF, colloidal silicon dioxide NF, magnesium stearate NF, hypromellose 2910 NF, titanium dioxide USP, polysorbate 80 NF, triacetin NF, FD&C blue 2 aluminum lake and yellow ferric oxide.

12 CLINICAL PHARMACOLOGY

12.1 Mechanism of Action

SLYND progestin-only oral contraceptive lowers the risk of becoming pregnant primarily by suppressing ovulation.

12.2 Pharmacodynamics

Drospirenone is a spironolactone analogue with anti-mineralocorticoid activity.

Laboratory Tests

The use of contraceptive steroids may influence the results of certain laboratory tests, including biochemical parameters of liver, thyroid, adrenal and renal function, serum levels of (carrier) proteins, e.g., corticosteroid binding globulin and lipid/lipoprotein fractions, parameters of carbohydrate metabolism and parameters of coagulation and fibrinolysis.

12.3 Pharmacokinetics

Absorption

The pharmacokinetics of oral drospirenone is dose-proportional following single doses ranging from 1-10 mg. Maximum concentrations (Cmax) of drospirenone in plasma of about 27 ng/ml are reached at about 2-6 hours after single ingestion of SLYND. During a treatment cycle, maximum steady-state concentrations of drospirenone in serum of about 41 ng/ml are reached after about 10 days of treatment. Plasma drospirenone Cmax and area under the curve (AUC) accumulate by a factor of about 1.5 to 2 following multiple dose administration of SLYND. Concomitant ingestion of food has no influence on the extent of absorption of drospirenone.

Distribution

Drospirenone is 95% to 97% bound to serum albumin and does not bind to sex hormone binding globulin (SHBG) or corticosteroid binding globulin (CBG). The apparent volume of distribution of drospirenone is approximately 4 L/kg

Elimination

Metabolism

Drospirenone is extensively metabolized after oral administration. The two main metabolites of DRSP found in human plasma were identified to be the acid form of DRSP generated by opening of the lactone ring and the 4,5-dihydrodrospirenone-3-sulfate, formed by reduction and subsequent sulfation. These metabolites were shown not to be pharmacologically active. Drospirenone is also subject to oxidative metabolism catalyzed by CYP3A4.

Excretion

DRSP serum concentrations are characterized by a terminal disposition phase half-life of approximately 30 hours after both single and multiple dose regimens. Excretion of DRSP was nearly complete after ten days and amounts excreted were slightly higher in feces compared to urine. DRSP was extensively metabolized and only trace amounts of unchanged DRSP were excreted in urine and feces.

Specific Populations

Patients with Hepatic Impairment:

The mean exposure to DRSP in females with moderate liver impairment is approximately three times higher than the exposure in females with normal liver function. SLYND has not been studied in females with severe hepatic impairment [see Contraindications (4) and Warnings and Precautions (5.5)].

Patients with Renal Impairment:

The effect of renal impairment on the pharmacokinetics of DRSP (3 mg daily for 14 days) and the effect of DRSP on serum potassium concentrations were investigated in three separate groups of female subjects (n = 28, age 30–65). All subjects were on a low potassium diet. During the study, 7 subjects continued the use of potassium-sparing drugs for the treatment of their underlying illness. On the 14th day (steady-state) of DRSP treatment, the serum DRSP concentrations in the group with CLcr of 50–79 mL/min were comparable to those in the control group with CLcr ≥ 80 mL/min. The serum DRSP concentrations were on average 37% higher in the group with CLcr of 30–49 mL/min compared to those in the control group. DRSP treatment did not show any clinically significant effect on serum potassium concentration. Although hyperkalemia was not observed in the study, in five of the seven subjects who continued use of potassium-sparing drugs during the study, mean serum potassium concentrations increased by up to 0.33 mEq/L. [See Contraindications (4) and Warnings and Precautions (5.1). ]

Drug Interaction Studies:

In a clinical drug-drug interaction study conducted in 20 premenopausal females, co-administration of a product containing DRSP (3 mg)/EE (0.02 mg) COC with the strong CYP3A4 inhibitor ketoconazole (200 mg twice daily) for 10 days increased the AUC(0-24h) and Cmax of DRSP by 2.68-fold (90% CI: 2.44, 2.95) and 1.97-fold (90% CI: 1.79, 2.17), respectively.

13 NONCLINICAL TOXICOLOGY

13.1 Carcinogenesis, Mutagenesis, Impairment of Fertility

In a 24-month oral carcinogenicity study in mice with doses up to 10 mg/kg/day DRSP, equating to 2 times the maximum clinical exposure (based on AUC), there was an increase in carcinomas of the harderian gland in the high dose DRSP group. In a similar study in rats given doses up to 10 mg/kg/day DRSP, 10 times the maximum clinical exposure (based on AUC), there was an increased incidence of benign and total (benign and malignant) adrenal gland pheochromocytomas in the high dose DRSP group. Mutagenesis studies for DRSP were conducted in vivo and in vitro and no evidence of mutagenic activity was observed.

14 CLINICAL STUDIES

Pregnancy Prevention

The efficacy of SLYND was evaluated in Study CF111/303 (NCT02269241). This single arm multicenter, clinical trial was conducted in the U.S. The efficacy population consisted of 953 females ≤ 35 years of age with 5,547 evaluable cycles. The demographic profile for females was: mean age 26.4 years and mean BMI 28.5 kg/m^2. The racial distribution was 53.3% Caucasian; 38.5% African American; 2.2% Asian and 6% other. During these cycles, a total of 17 (1.8%) females reported pregnancy, leading to a Pearl Index (95% CI) of 4.0 (2.3, 6.4).

One female who became pregnant during the study was breastfeeding and not included in the Pearl Index (PI) calculation. The confidence interval for the PI was calculated assuming that events of pregnancy had a Poisson distribution.

Out of the 953 females evaluated for efficacy, 332 subjects had a baseline BMI ≥ 30 (35%) and 173 females had a baseline BMI ≥ 35 (18%). Data were insufficient to analyze PI by BMI subgroups.

Table 4 Pearl Index Based on Evaluable Cycles and Reported Pregnancies in Females ≤ 35 Years of Age in Study CF111/303
 | SLYND (N = 953)
Subjects with pregnancy, n (%) | 17 (1.8)
Subjects without pregnancy, n (%) | 936 (98.2)
Total number of evaluable cycles | 5547
Pearl Index for evaluable cycles | 4.0
95% Confidence Interval for Pearl Index, Lower Limit, Upper Limit | 2.3, 6.4

Effect on Bleeding Patterns

The bleeding pattern with SLYND was assessed systematically using patient diaries in Study CF111/303 in adult females.

The percentage of females experiencing scheduled bleeding or unscheduled bleeding/spotting decreased over time. Overall, the percentage of females with scheduled bleeding or spotting decreased from 81% in Cycle 1 to 26% in Cycle 13. Similarly, the overall percentage of females with unscheduled bleeding or spotting decreased from 61% in Cycle 1 to 40% in Cycle 13. The percentages of females with scheduled and unscheduled bleeding or spotting generally decreased through Cycle 10 and were maintained at a consistent level thereafter.

Table 5 Adult Females with Scheduled and Unscheduled Bleeding or Spotting: (Safety Set)
 | Scheduled |  | Unscheduled
Cycle | n/m [Abbreviations: m = number of subjects with cycle data; n = number of subjects with bleeding or spotting.] | Rate and 95% CI (%) | n/m | Rate and 95% CI (%)
Cycle 1 | 1768/2178 | 81.2 (79.5, 82.8) | 1337/2178 | 61.4 (59.3, 63.4)
Cycle 6 | 507/1482 | 34.2 (31.8, 36.6) | 703/1482 | 47.4 (44.9, 50.0)
Cycle 13 | 185/700 | 26.4 (23.2, 29.7) | 282/700 | 40.3 (36.7, 43.9)

In Study CF111/304 conducted in Europe in post-menarchal, female, adolescents (12 through 17 years of age), bleeding data were generally consistent with those from Study CF111/303 in adult females. SLYND was associated with a decrease in the percentage of adolescent females experiencing bleeding or spotting over time. The percentage of adolescent females with scheduled bleeding or spotting decreased from 98.0% in Cycle 1 to 28.4% in Cycle 13. The percentage of adolescent females with scheduled bleeding or spotting generally decreased through Cycle 9 and was maintained at a consistent level thereafter. In contrast, the percentage of adolescent females with unscheduled bleeding or spotting was maintained at a relatively consistent level during the study (53.0% in Cycle 1 versus 52.2% in Cycle 13).

In addition to Studies CF111/303 and CF111/304, two additional studies evaluated bleeding associated with SLYND. A total of 91 females (3.5%) from these four studies discontinued SLYND due to problems with irregular bleeding or amenorrhea.

16 HOW SUPPLIED/STORAGE AND HANDLING

16.1 How Supplied

SLYND (drospirenone) tablets is packaged in clear to a slightly opaque PVC-PVDC/Aluminum blister cards. Each blister card holds 24 white round active film-coated tablets, each containing 4mg of drospirenone and 4 green round inert film-coated tablets that do not contain drospirenone. SLYND is supplied in cardboard cartons containing a blister card of 28 tablets: NDC 0642-7470-01.

16.2 Storage and Handling

Store at 25°C (77°F); excursions permitted from 15 to 30°C (59 to 86°F) [ see USP Controlled Room Temperature].

17 PATIENT COUNSELING INFORMATION

Advise the patient to read the FDA-approved Patient Labeling (Patient Information and Instructions for Use).

SLYND and Dosing Instructions

Advise females on proper daily use of SLYND and what to do if she misses a pill [see Dosage and Administration (2) and FDA-approved Patient Information] . Inform patient that amenorrhea may occur and instruct patient to check for pregnancy if she misses two consecutive periods.

Counsel patients on the following information

Recommendation to check serum potassium levels during the first treatment cycle in females receiving daily, long-term treatment for chronic conditions of diseases with medications that may increase serum potassium concentrations

Sexually Transmitted Infections

SLYND does not protect against HIV-infection (AIDS) and other sexually transmitted infections.

Use during Pregnancy

SLYND is not to be used during pregnancy; instruct the patient to stop use if pregnancy is confirmed during treatment [see Use in Specific Populations (8.1)].

Drug Interactions

Advise females to inform their healthcare provider if they take herbal supplements such as St. John's wort [see Drug Interactions (7.1)].

Distributed by:

Exeltis USA, Inc. Florham Park, NJ 07932

© 2025 All rights reserved. Slynd is a registered trademark of Chemo Research SL

PATIENT INFORMATION SLYND (slind) (drospirenone) tablets, for oral use

Progestin pills help to lower the chance of becoming pregnant when taken as directed. They do not protect against HIV infection (AIDS) and other sexually transmitted diseases (STDs).

What is SLYND?

SLYND is a birth control pill (oral contraceptive) also called a POP (progestin only pill) that is used by females who can become pregnant to prevent pregnancy.

The progestin drospirenone may increase potassium levels in your blood. You should not take SLYND if you have kidney, liver or adrenal disease because this could cause serious heart problems as well as other health problems. Other medicines may also increase potassium levels in your blood. If you are currently on daily, long-term treatment for a chronic health condition with any of the medicines listed below, talk to your healthcare provider about whether SLYND is right for you. If you take any of the medicines listed below for a chronic health condition you should have a blood test to check the potassium level in your blood before you start taking SLYND and during the first month that you take SLYND.

- medicines to treat fungal infections, such as ketoconazole, itraconazole, or voriconazole
- medicines to treat Human Immunodeficiency Virus (HIV) infection or Hepatitis C infection, such as indinavir or boceprevir
- clarithromycin

How does SLYND work for contraception?

Your chance of getting pregnant depends on how well you follow the directions for taking your birth control pills. The better you follow the directions, the less chance you have of getting pregnant.

Based on the results of one clinical study of a 28-day regimen of SLYND about 4 out of 100 females may get pregnant within the first year they use SLYND.

The following chart shows the chance of getting pregnant for females who use different methods of birth control. Each box on the chart contains a list of birth control methods that are similar in effectiveness. The most effective methods are at the top of the chart. The box on the bottom of the chart shows the chance of getting pregnant for females who do not use birth control and are trying to get pregnant.

Do not take SLYND if you:

- have kidney disease or kidney failure.
- have reduced adrenal gland function (adrenal insufficiency).
- have or have had cervical cancer or any cancer that is sensitive to female hormones.
- have liver disease, including liver tumors.
- have unexplained vaginal bleeding.

Tell your healthcare provider if you have or have had any of these conditions. Your healthcare provider can suggest a different method of birth control.

If any of these conditions happen while you are taking SLYND, stop taking SLYND right away and talk to your healthcare provider. Use non-hormonal contraception when you stop taking SLYND.

Before you take SLYND, tell your healthcare provider about all of your medical conditions, including if you:

- are pregnant or think you may be pregnant.
- have ever had blood clots in your legs (deep vein thrombosis), lungs (pulmonary embolism) or a stroke or heart attack (myocardial infarction).
- have or have had depression

Tell your healthcare provider about all the medicine you take including prescription and over-the-counter medicines, vitamins and herbal supplements, such as St. John's Wort.

SLYND may affect the way other medicines work, and other medicines may affect how well SLYND works.

Know the medicines you take. Keep a list of them to show your healthcare provider and pharmacist when you get a new medicine.

How should I take SLYND?

Read the detailed Instructions for Use at the end of this Patient Information leaflet about the right way to take SLYND.

What are the possible serious side effects of SLYND?

SLYND may cause serious side effects, including:

- High potassium levels in your blood (hyperkalemia). Certain medicines and conditions can also increase the potassium levels in your blood. Your healthcare provider may check the potassium levels in your blood before and during treatment with SLYND. Call you healthcare provider or go to a hospital emergency room right away if you have signs or symptoms of high potassium levels in your blood including:
  - weakness or numbness in an arm or leg
- palpitations (feel like your heart is racing or fluttering) or irregular heartbeat
- nausea
- vomiting
- severe pain in your chest
- shortness of breath
- Blood clot forming in blood vessels (thromboembolism problems). Tell your healthcare provider if you have had a blood clot. Tell your healthcare provider if you plan to have surgery or are not able to be active due to illness or injury. Call your healthcare provider or go to a hospital emergency room right away if you have:
  - leg pain that will not go away
  - a sudden, severe headache unlike your usual headaches
  - sudden, severe shortness of breath
  - sudden change in vision or blindness
  - chest pain
  - weakness or numbness in your arm or leg
  - trouble speaking
- Bone loss. It is not known if the decrease in a sex hormone that happens with SLYND can result in decreased bone density (bone loss).
- Cervical cancer. See " Do birth control pills cause cancer?"
- Liver problems, including rare liver tumors. Call your healthcare provider right away if you have yellowing of your skin or eyes.
- Ectopic pregnancy (pregnancy in your tubes). If you get pregnant while using SLYND, you might have an ectopic pregnancy. That means that the pregnancy is not in the uterus. Ectopic pregnancy is a medical emergency that often requires surgery. If you have severe abdominal (belly) pain, call your healthcare provider or go to a hospital emergency room right away.
- Risk of high blood sugar levels in people with diabetes. If you have diabetes, you may need to monitor your blood sugar level more often or adjust your diabetes medicine.
- Changes in menstrual bleeding. Irregular vaginal bleeding, especially between menstrual periods, and irregular periods or the absence of menstrual periods are common side effects of SLYND, but can sometimes be serious. Tell your healthcare provider if you have any of these changes in menstrual bleeding.
- Depression, especially if you have had depression in the past. Call your healthcare provider immediately if you have any thoughts of harming yourself.

What are the most common side effects of SLYND?

The most common side effects of SLYND include:

- acne
- headache
- breast pain and tenderness
- weight gain

- menstrual cramps
- nausea
- severe vaginal bleeding
- less sexual desire

These are not all the possible side effects of SLYND.

Call your doctor for medical advice about side effects. You may report side effects to FDA at 1-800-FDA-1088.

What else should I know about taking SLYND?

- If you are scheduled for any lab tests, tell your healthcare provider you are taking SLYND. Certain blood tests may be affected by SLYND.

How should I store SLYND?

- Store SLYND at room temperature between 68°F to 77°F (20°C to 25°C).
- Keep SLYND and all medicines out of the reach of children.

General information about the safe and effective use of SLYND.

Medicines are sometimes prescribed for purposes other than those listed in a Patient Information leaflet. Do not use SLYND for a condition for which it was not prescribed. Do not give SLYND to other people, even if they have the same symptoms that you have. It may harm them. You can ask your pharmacist or healthcare provider for information about SLYND that is written for health professionals.

Do birth control pills cause cancer?

Hormonal contraceptives do not appear to cause breast cancer. However if you have breast cancer now, have had it in the past, or you have (or have had) another cancer that may be sensitive to hormones, do not use hormonal contraceptives.

Women who use hormonal contraceptives may have a higher chance of getting cervical cancer. However, this may be due to other reasons such as having more sexual partners and exposure to the human papilloma virus (HPV).

What if I want to become pregnant?

You may stop taking SLYND whenever you wish. Consider a visit with your healthcare provider for a pre-pregnancy checkup before you stop taking SLYND.

What should I know about my period when taking SLYND?

Some females may miss a period. Irregular vaginal bleeding or spotting may happen while you are taking SLYND, especially during the first few months of use. If the irregular vaginal bleeding or spotting continues or happens again after you have had regular menstrual cycles call your healthcare provider. It is important to continue taking your pills on a regular schedule to prevent a pregnancy.

What if I miss my scheduled period when using SLYND?

Some females miss periods on hormonal birth control, even when they are not pregnant. However, if you go 2 or more months in a row without a period, or you miss your period after a month where you did not use all of your SLYND correctly, call you healthcare provider because you may be pregnant. Also call your healthcare provider if you have symptoms of pregnancy such as morning sickness or unusual breast tenderness. Stop taking SLYND if you are pregnant.

What are the ingredients in SLYND?

White tablets

Active ingredient: drospirenone

Inactive ingredients: microcrystalline cellulose, anhydrous lactose, colloidal silicon dioxide, magnesium stearate, polyvinyl alcohol partially hydrolyzed, talc, titanium dioxide, and polyethylene glycol.

Green tablets

Inactive ingredients: lactose monohydrate, corn starch, povidone 30000, colloidal
silicon dioxide, magnesium stearate, hypromellose 2910, titanium dioxide, polysorbate 80, triacetin, FD&C blue 2 aluminum lake, and yellow ferric oxide.

Instructions For Use SLYND (slind) (drospirenone) tablets, for oral use

Important Information about taking SLYND

Before you start taking SLYND

- Decide what time of day you want to take your pill. It is important to take it at the same time every day and in the order as directed on your blister pack.
- Have backup contraception (condoms or spermicide) available.

How to take SLYND

- Take 1 pill every day at the same time. Take the pills in the order directed on your blister pack.
- Both the white pills and the green pills should be swallowed whole.
- Do not skip your pills, even if you do not have sex often. If you miss pills (including starting the blister pack late) you could get pregnant. The more pills you miss, the more likely you are to get pregnant.
- If you have trouble remembering to take SLYND, talk to your healthcare provider. When you first start taking SLYND, spotting or light bleeding in between your periods may occur. Contact your healthcare provider if this does not go away after a few months.
- You may feel sick to your stomach (nauseous), especially during the first few months of taking SLYND. If you feel sick to your stomach, do not stop taking the pill. The problem will usually go away. If your nausea does not go away, call your healthcare provider.
- Missing pills can also cause spotting or light bleeding, even when you take the missed pills later. On the days you take 2 pills to make up for missed pills (see below), you could also feel a little sick to your stomach.
- Some females miss periods on hormonal birth control, even when they are not pregnant. However, if you miss a period and have not taken SLYND according to directions, or miss 2 periods in a row, or feel like you may be pregnant, call your healthcare provider. If you have a positive pregnancy test, you should stop taking SLYND.
- If you have vomiting or diarrhea within 3 to 4 hours of taking your pill, take a new pill (the pill scheduled for the next day) from your blister pack within 12 hours of the usual time you take your pill, if possible. Continue taking all your remaining pills in order. Start the first pill of your next blister pack the day after finishing your current blister pack. This will be 1 day earlier than originally scheduled. Continue on your new schedule.
- If you have vomiting or diarrhea for more than 1 day, your birth control pills may not work as well. If you have sex within 7 days after 1 or more days of vomiting or having diarrhea, use an additional form of birth control, like condoms or spermicide, as back-up contraception.

When should I start taking SLYND?

If you start taking SLYND and you are not currently using a hormonal birth control method:

- Start SLYND on the first day (Day 1) of your natural menstrual period (Day 1 Start). Your healthcare provider should tell you when to start taking your birth control pill.

If you start taking SLYND and you are switching from another birth control pill:

- Start your new SLYND blister pack on the same day that you would start the next pack of your previous birth control method.
- Do not continue taking the pills from your previous birth control pack.

If you start taking SLYND and you are switching from a vaginal ring or transdermal patch:

- Start taking SLYND on the day you would have inserted the next ring or applied the next patch.

If you start taking SLYND and you are switching from a progestin-only method such as an implant or injection:

- Start taking SLYND on the day of removal of your implant or on the day when you would have had your next injection.

If you start taking SLYND and you are switching from an intrauterine device or system (IUD or IUS):

- Start taking SLYND on the day of removal of your IUD or IUS.

Keep a calendar to track your period:

SLYND Day 1 Start:

You will use a Day 1 Start if your healthcare provider told you to take your first pill (Day 1) on the first day of your period.

- Take 1 pill every day in the order of the blister pack, at the same time each day, for 28 days.
- After taking the last pill on Day 28 from the blister pack, start taking the first pill from a new pack, on the same day of the week as the first pack. Take the first pill in the new pack whether or not you are having your period.

Instructions for using your pill blister pack:

Step 1. Look at your SLYND pill pack. See Figure A.

The SLYND pill pack has:

- 24 white (active) pills with hormone for Week 1 through Week 3 and the first 3 days of Week 4 (Days 1-24)
- 4 green (inactive) pills without hormones for the last 4 days of Week 4 (Days 25-28).

FIGURE A

Step 2.

Place the day label strip (see Figure B) that starts with the first day of your period (Day 1) on top of the pill blister pack over "Place the label here". See Figure C. For example, if your period begins on Monday, place the day label strip with Monday as the first day on the top of your pill pack. See Figure C.

FIGURE B

FIGURE C

Step 3.

Remove the white pill by pressing the pill through the foil in the bottom of the pill blister pack. Continue taking the white pills for 24 days.

Step 4.

In the middle of Week 4 start taking the green pills. Take the green pill for 4 days. Your period should start during this time.

Step 5.

When you have taken all of the green pills in your pill pack, get a new pill pack and start taking the white pills from the new pill blister pack at your usual time the following day, starting with the Day 1 pill.

For a Day 1 start:

- Begin your next pill pack on the same day of the week as your first cycle pill pack.

What should I do if I miss any SLYND pills?

If you miss 1 white pill (active pills):

- Take it as soon as you remember. Take the next pill at your regular time. This means you may take 2 pills in 1 day.
- Then continue taking 1 pill every day until you finish the pack.
- You do not need to use a back-up birth control method if you have sex.

If you miss 2 or more white pills (active pills), follow these steps:

- Take a pill as soon as you remember. Take the next pill at your regular time. This means you may take 2 pills in 1 day.
- Then continue to take 1 pill every day until you finish the pack (this will mean one or more missed white pills will remain in the blister pack).
- Use a non-hormonal birth control method (such as a condom or spermicide) as a back-up if you have sex during the first 7 days after missing your pills.

If you miss 1 or more green pills (inactive pill):

- You do not need to take 1 or more missed green pills. Take the next green pill at your regular time, every day until you finish the pack (this means 1 or more missed green pill will remain in the blister pack).

If you have any questions or are unsure about the information in this leaflet, call your healthcare provider. You can ask your healthcare provider or pharmacist for information about SLYND that is written for health professionals.

This Patient Information and Instructions for Use has been approved by the U.S. Food and Drug Administration.

Distributed by: Exeltis USA, Inc. Florham Park, NJ 07932

© 2025 All rights reserved. Slynd is a registered trademark of Chemo Research SL.

Revised: 06/2025 4700101-04

PRINCIPAL DISPLAY PANEL - 4 mg Tablet Blister Card Carton

NDC 0642-7470-01

Rx only

Slynd®
(drospirenone) tablets, 4 mg

1 blister card with 28 tablets / Oral Use Exeltis

THIS PRODUCT (LIKE ALL ORAL CONTRACEPTIVES) IS INTENDED TO PREVENT PREGNANCY. IT DOES

NOT PROTECT AGAINST HIV INFECTION (AIDS) AND OTHER SEXUALLY TRANSMITTED DISEASES.